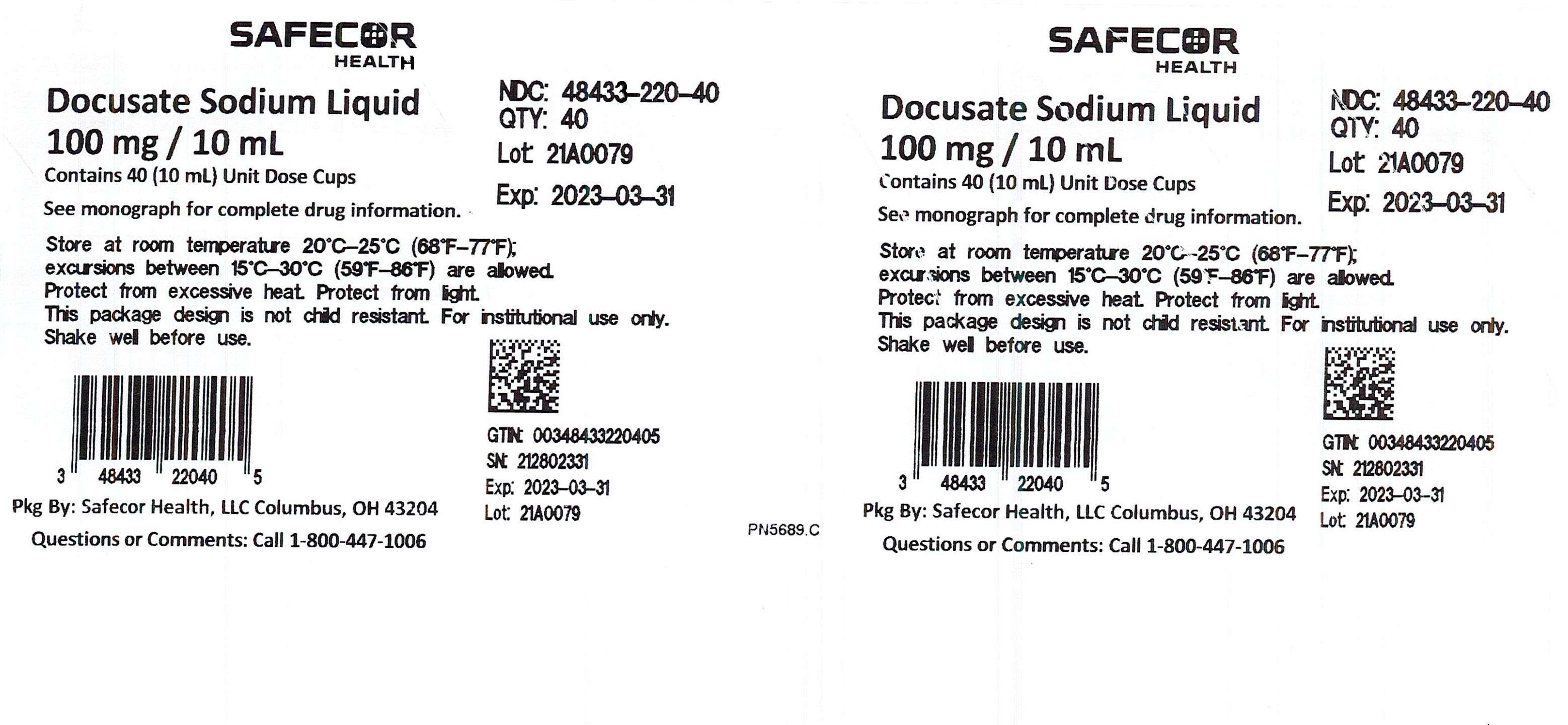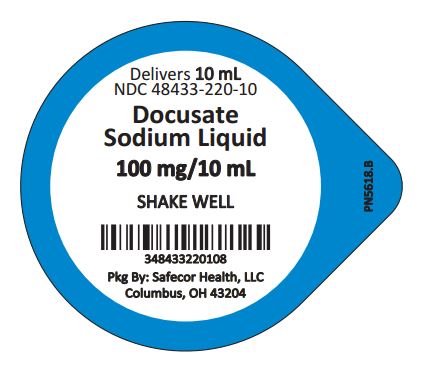 DRUG LABEL: DOCUSATE SODIUM
NDC: 48433-220 | Form: LIQUID
Manufacturer: Safecor Health, LLC
Category: otc | Type: HUMAN OTC DRUG LABEL
Date: 20250108

ACTIVE INGREDIENTS: DOCUSATE SODIUM 50 mg/5 mL
INACTIVE INGREDIENTS: FD&C RED NO. 40; METHYLPARABEN; POLOXAMER 124; POLYETHYLENE GLYCOL, UNSPECIFIED; PROPYLENE GLYCOL; PROPYLPARABEN; WATER; SODIUM BENZOATE; SODIUM CITRATE; SUCRALOSE

SAFECOR HEALTH
Docusate Sodium Liquid
Drug Facts

Active Ingredient (in each 5 mL = 1 teaspoonful)

Docusate Sodium 50 mg

Purpose

Stool Softener

Use:

Relief of occasional constipation

WARNINGS:

Do not use * when abdominal pain, nausea, or vomiting are present * for a period longer than 1 week unless directed by a doctor

Ask a doctor before use if you * have noticed a sudden change in bowel habits that persist over a period of 2 weeks * are taking mineral oil

Stop use and ask a doctor if you have rectal bleeding or failure to have a bowel movement within 3 days.

These could be signs of a serious condition. * a skin rash occurs * you experience throat irritation

PREGNANCY OR BREAST FEEDING

If pregnant or breast feeding, ask a health care professional before use.

KEEP OUT OF REACH OF CHILDREN

Keep this and all drugs out of reach of children. In case of overdose, get medical help or contact a Poison Control Center immediately. In case of eye contact, flush with water.

Directions:
* Must be given in a 6 oz to 8 oz glass of milk or fruit juice to prevent throat irritation
* Shake well before using
* Do not exceed recommended dose
* May be taken in one to four equally divided oral doses each day
* Take maximum dose daily until first bowel movement, dosage should then be reduced according to individual response
Adults and children 12 years of age and over | 5 mL (1 teaspoon) to 40 mL (8 teaspoons) or as directed by a doctor
Children 6 to 12 years of age | 4 mL to 15 mL (3 teaspoons) or as directed by a doctor
Children 3 to 6 years of age | 2 mL to 6 mL or as directed by a doctor
Children under 3 years of age | 1 mL to 4 mL or as directed by a doctor

1 teaspoon = 5 mL

Other information: Each teaspoon (5 mL) contains: sodium 5 mg. Store at room temperature 20°C-25°C (68°F-77°F); excursions
between 15°C-30°C (59°F-86°F) are allowed. Protect from excessive heat. Protect from light. For more info call 1-800-447-1006.

INACTIVE INGREDIENT

Inactive ingredients: FD&C red #40, flavor, methylparaben, poloxamer, polyethylene glycol, propylene glycol, propylparaben, purified
water, sodium benzoate, sodium citrate, and sucralose.

NDC: 48433-220-10 Docusate Sodium Liquid 100 mg/10 mL Unit Dose Cup

Mfd. in the U.S.A.
Distributed by: Safecor Health, LLC
4060 Business Park Drive, Columbus, OH 43204 Rev: 11/2020 PN5473

3 4843322010 8

Principal Display Panel - Box Label

SAFECOR
HEALTH
Docusate Sodium Liquid
100 mg / 10 ml
Contains 40 (10 ml) Unit Dose Cups

See monograph for complete drug information.

NDC: 48433-220-40
QTY: 40
Lot: 21A0079
Exp: 2023-03-31

Store at room temperature 20°C-25°C (68°F-77°F);
excursions between 15°C-30°C (59°F-86°F) are allowed.
Protect from excessive heat. Protect from light.
This package design is not child resistant. For institutional use only.
Shake well before use.

3 48433 22040 5
Pkg By: Safecor Health, LLC Columbus, OH 43204
Questions or Comments: Call 1-800-447-1006

GTIN: 00348433220405
SN: 212802331
Exp; 2023-03-31
Lot 21A0079 PN5689.C

Principal Display Panel - Lid Label

Delivers 10 mL

NDC 48433-220-10

Docusate

Sodium Liquid

100 mg/10mL

SHAKE WELL

348433220108

Pkg By: Safecor Health, LLC

Columbus, OH 43204

PN5618.B